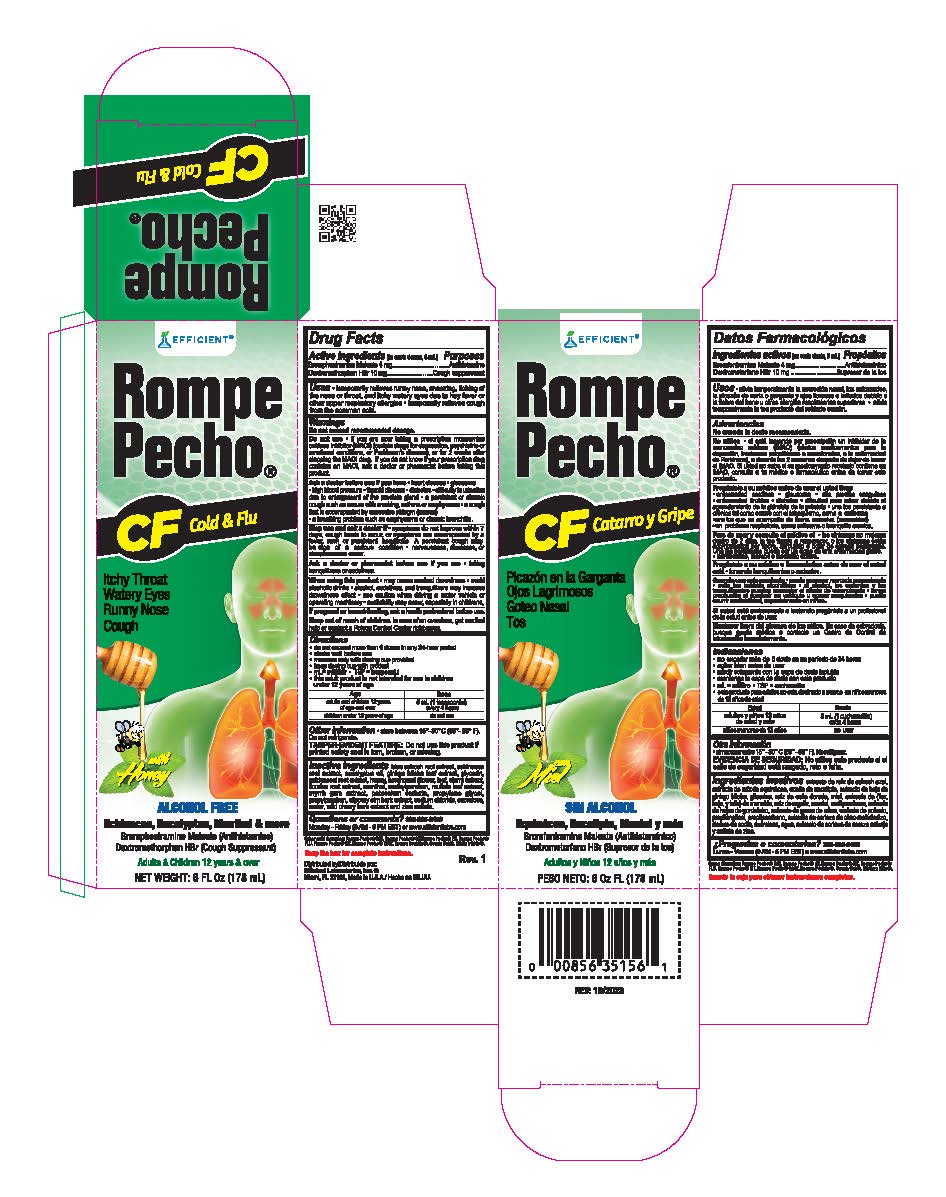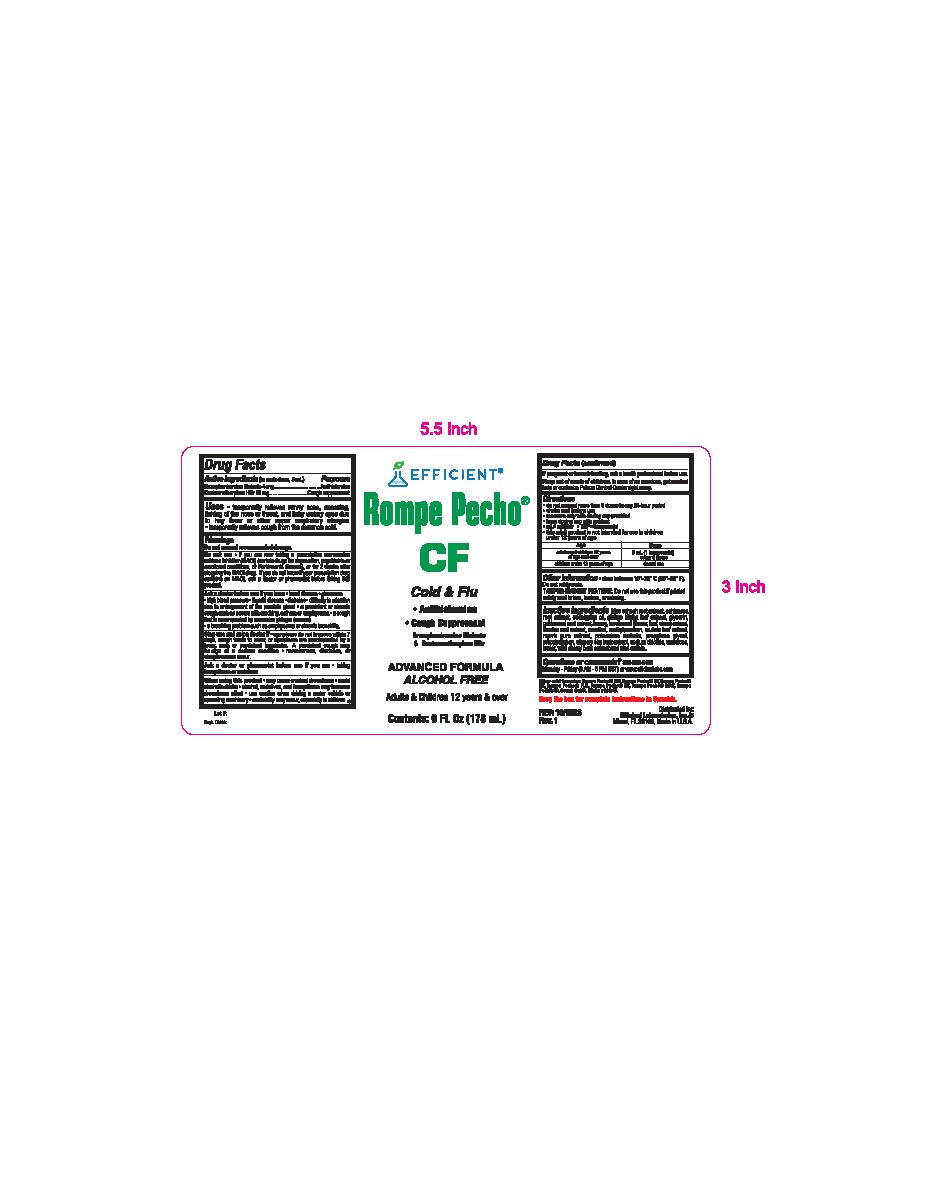 DRUG LABEL: Rompe Pecho CF

NDC: 58593-001 | Form: LIQUID
Manufacturer: Efficient Laboratories Inc
Category: otc | Type: HUMAN OTC DRUG LABEL
Date: 20241008

ACTIVE INGREDIENTS: DEXTROMETHORPHAN HYDROBROMIDE 10 mg/5 mL; BROMPHENIRAMINE MALEATE 4 mg/5 mL
INACTIVE INGREDIENTS: CAULOPHYLLUM THALICTROIDES ROOT; GLYCERIN; ECHINACEA ANGUSTIFOLIA ROOT; EUCALYPTUS OIL; GINKGO BILOBA LEAF OIL; GOLDENSEAL; HONEY; HOREHOUND; MENTHOL; METHYLPARABEN; LICORICE; MULLEIN LEAF; POTASSIUM SORBATE; PROPYLENE GLYCOL; PROPYLPARABEN; WATER; ULMUS RUBRA BARK; SODIUM CHLORIDE; PRUNUS SEROTINA BARK; ZINC SULFATE; MYRRH; SUCRALOSE

Rompe Pecho CF

Active Ingredients:(in each teaspoonful 5 ml.) Purpose

Brompheniramine Maleate 4mg ................................................ Antihistamine

Dextromethorphan HBr 10 mg .................................................... Cough Suppressant

Purpose

Antihistamine

Cough Suppressant

Warnings

Do not exceed recommended dosage.

Do not use

- If you are taking a prescription monoamine oxidase inhibitor (MAOI) (certain drugs for depression, psychiatric, or
  emotional conditions or Parkinson’s disease), or for 2 weeks after stopping the MAOI drug. If you do not know if your prescription drug contains an MAOI; ask your doctor or pharmacist before taking this product.

Ask a doctor before use if you have
• heart disease

- glaucoma

• high blood pressure

• thyroid disease

• diabetes

• difficulty in urination due to an enlarged prostate gland

• a persistent or chronic cough such as occurs with smoking, asthma, or emphysema

- a cough that is accompanied by excessive phlegm (mucus)

• a breathing problem such as emphysema or chronic bronchitis

Stop use and ask doctor if

- symptoms do not improve within 7 days, cough tends to recur, or symptoms are accompanied by a fever, rash or persistent headache. A persistent cough may be sign of a serious condition.
- nervousness, dizziness, or sleeplessness occurs

PREGNANCY OR BREAST FEEDING

If pregnant or breast-feeding,ask a health professional before use.

Keep out of reach of children.In case of accidental overdose, get medical help or contact a Poison Control Center right away.

Directions

- Do not exceed more than 6 doses in any 24-hour period
- Shake well before use
- measure only with dosing cup provided
- keep dosing cup with product
- mL=miliiter TSP=teaspoonful
- this adult product is not intended for use in children under 12 years of age

Age | - Dose
- adults and children 12 years of age and over | - 5 mL (1 teaspoonfuls) every 4 hours
- children under 6 years of age | - do not use

Uses

- temporarily relieves runny nose, sneezing, itching of the nose or throat, and itchy watery eyes due to hay fever or other upper respiratory allergies
- temporarily relieves cough from the common cold

INACTIVE INGREDIENT

Inactive Ingredients:Blue Cohosh root extract, Echinacea root extract, Eucalyptus Oil, Ginkgo Biloba leaf extract, glycerin, Golden Seal root extract, Honey, Horehound (flower, leaf, stem) extract, Licorice Root extract, Menthol, Methylparaben, Mullein leaf extract, Myrrh gum extract, Potassium Sorbate, Propylene Glycol, Propylparaben, Slippery Elm Bark extract, Sodium Chloride, Sucralose, Water, Wild Cherry Bark extract and Zinc Sulfate.

Questions or Comments?

305-805-3456 Monday - Friday 9AM to 5PM EST

www.efficientlabs.com

Distributed by

Efficient Laboratories, Inc., Miami, Fl 33166

Made in U.S.A.